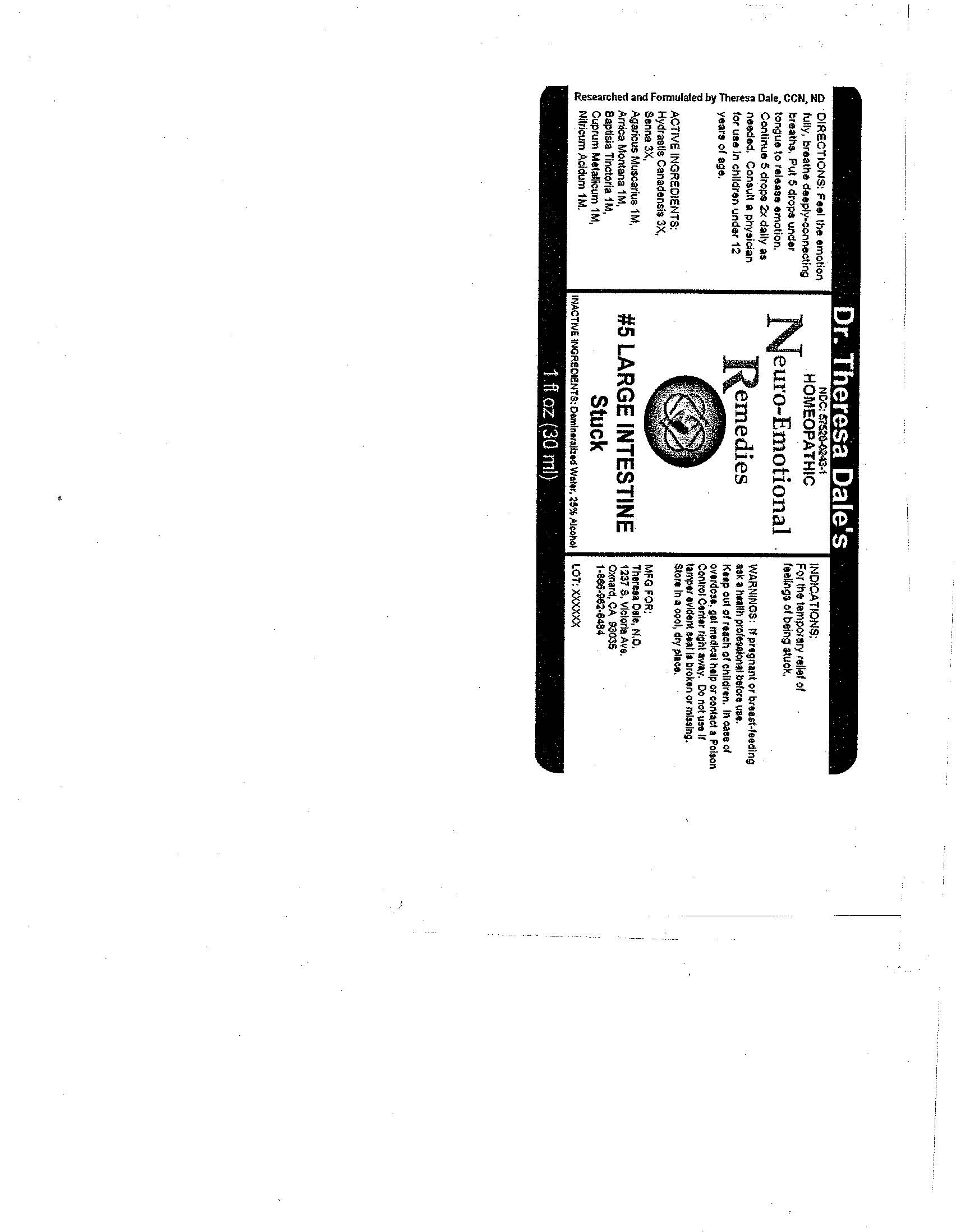 DRUG LABEL: 5 Large Intestine
NDC: 57520-0243 | Form: LIQUID
Manufacturer: Apotheca Company
Category: homeopathic | Type: HUMAN OTC DRUG LABEL
Date: 20100802

ACTIVE INGREDIENTS: GOLDENSEAL 3 [hp_X]/1 mL; SENNA LEAF 3 [hp_X]/1 mL; AMANITA MUSCARIA VAR. MUSCARIA 1 [hp_M]/1 mL; ARNICA MONTANA 1 [hp_M]/1 mL; BAPTISIA TINCTORIA ROOT 1 [hp_M]/1 mL; COPPER 1 [hp_M]/1 mL; NITRIC ACID 1 [hp_M]/1 mL
INACTIVE INGREDIENTS: WATER; ALCOHOL

#5 Large Intestine

ACTIVE INGREDIENT

ACTIVE INGREDIENTS: Hydrastis canadensis 3X, Senna 3X, Agaricus muscarius 1M, Arnica montana 1M, Baptisia tinctoria 1M, Cumprum metallicum 1M, Nitricum acidum 1M.

PURPOSE

INDICATIONS: For the temporary relief of feelings of being stuck.

WARNINGS

WARNINGS: If pregnant or breast-feeding, ask a health professional before use.

Keep out of reach of children. In case of overdose, get medical help or contact a Poison Control Center right away.

Do not use if tamper evident seal is broken or missing. Store in a cool, dry place.

DOSAGE AND ADMINISTRATION

DIRECTIONS: Feel the emotion fully, breathe deeply-connecting breaths. Put 5 drops under tongue to release emotion. Continue 5 drops 2x daily as needed. Consult a physician for use in children under 12 years of age.

INACTIVE INGREDIENTS: Demineralized water, 25% Alcohol.

QUESTIONS

MFG FOR:

Theresa Dale, N.D.

1237 S. Victoria Ave.

Oxnard, CA 93035

PACKAGE LABEL

Dr. Theresa Dale's

HOMEOPATHIC

Neuro-Emotional Remedies

#5 LARGE INTESTINE

Stuck
1 fl oz (30 ml)